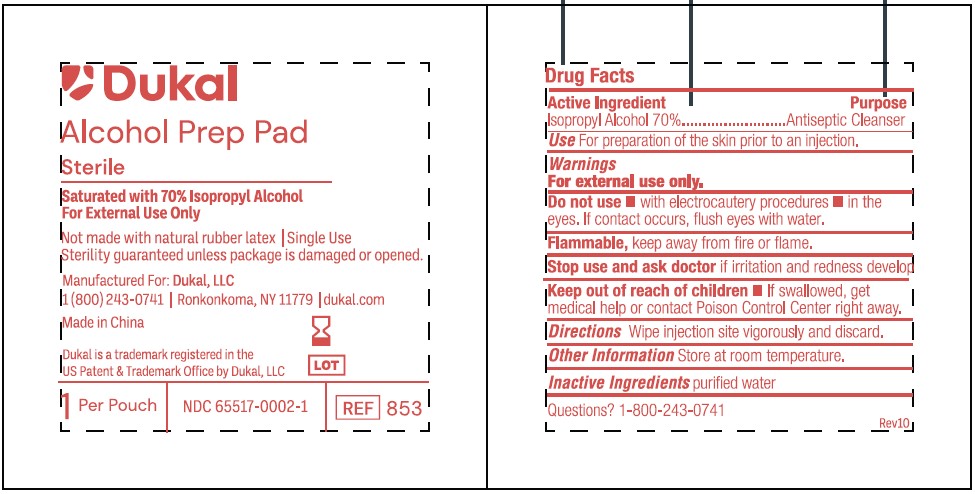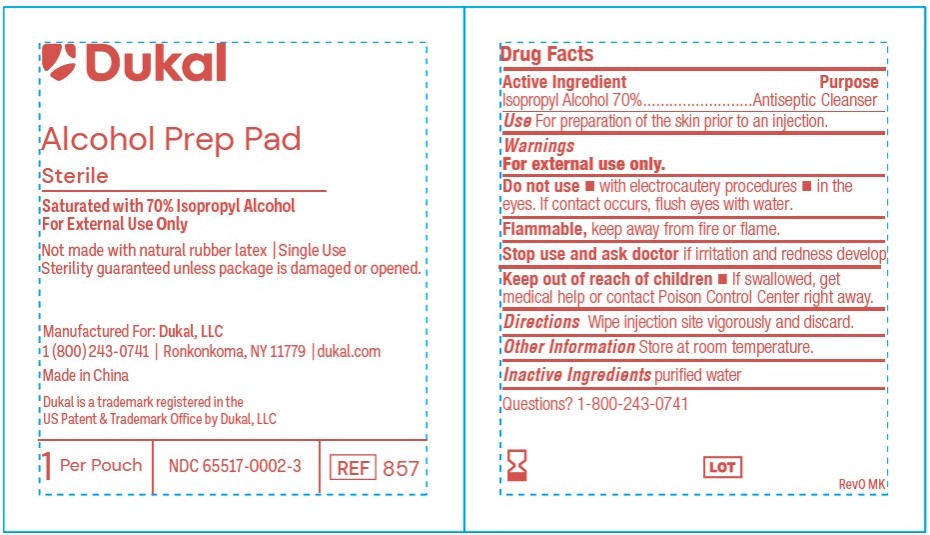 DRUG LABEL: Dukal Sterile Alcohol Prep Pad
NDC: 65517-0002 | Form: SWAB
Manufacturer: Dukal LLC
Category: otc | Type: HUMAN OTC DRUG LABEL
Date: 20250423

ACTIVE INGREDIENTS: ISOPROPYL ALCOHOL 0.7 mL/1 mL
INACTIVE INGREDIENTS: WATER

65517-0002 - Alcohol Prep Pad

Drug Facts

Active Ingredients

Isopropyl Alcohol 70%

Purpose

Antiseptic Cleanser

Use

For Preparation of Skin prior to an injection

INDICATIONS AND USAGE

For preparation of the skin prior to injection

Indications & Usage Section

Updated to match label claim

Warnings

- For External Use Only
- Flammable, Keep away from fire or flame

Do Not Use

- with electrocautery procedures
- In the Eyes. If contact occurs, flush eyes with water

Stop Use

If irritation and redness develop. If condition persists, consult your health care practitioner.

Keep out of reach of children

If swallowed, get medical help or contact a Poison Control Center right away.

Other Information

Store at Room Temperature 15 - 30 C (59 - 86 F)

Other Information

Store at Room Temperature 15 - 30 C (59 - 86 F)

Inactive Ingredient

purified water

PACKAGE LABEL

Dukal

Alcohol Pad

Sterile

Saturated with 70% Isopropyl Alcohol

For External Use Only

Not made with natural rubber latex / Single Use

Sterility guaranteed unless package is damaged or opened

Manufactured For: Dukal, LLC

1(800)243-0741 /Ronkonkoma, NY 11779 / dukal.com

Made in China

Dukal is a trademark registered in the

US Patent & Trademark Office by Dukal, LLC

1 Per Pouch / NDC 65517-0002-1 / REF 853

PACKAGE LABEL

Dukal

Alcohol Prep Pad

Sterile

Saturated with 70% Isopropyl Alcohol

For External Use Only

Not made with natural rubber latex / Single Use

Sterility guaranteed unless package is damaged or opened

Manufactured For: Dukal, LLC

1(800)243-0741 /Ronkonkoma, NY 11779 / dukal.com

Made in China

Dukal is a trademark registered in the

US Patent & Trademark Office by Dukal, LLC

1 Per Pouch / NDC 65517-0002-3 / REF 857